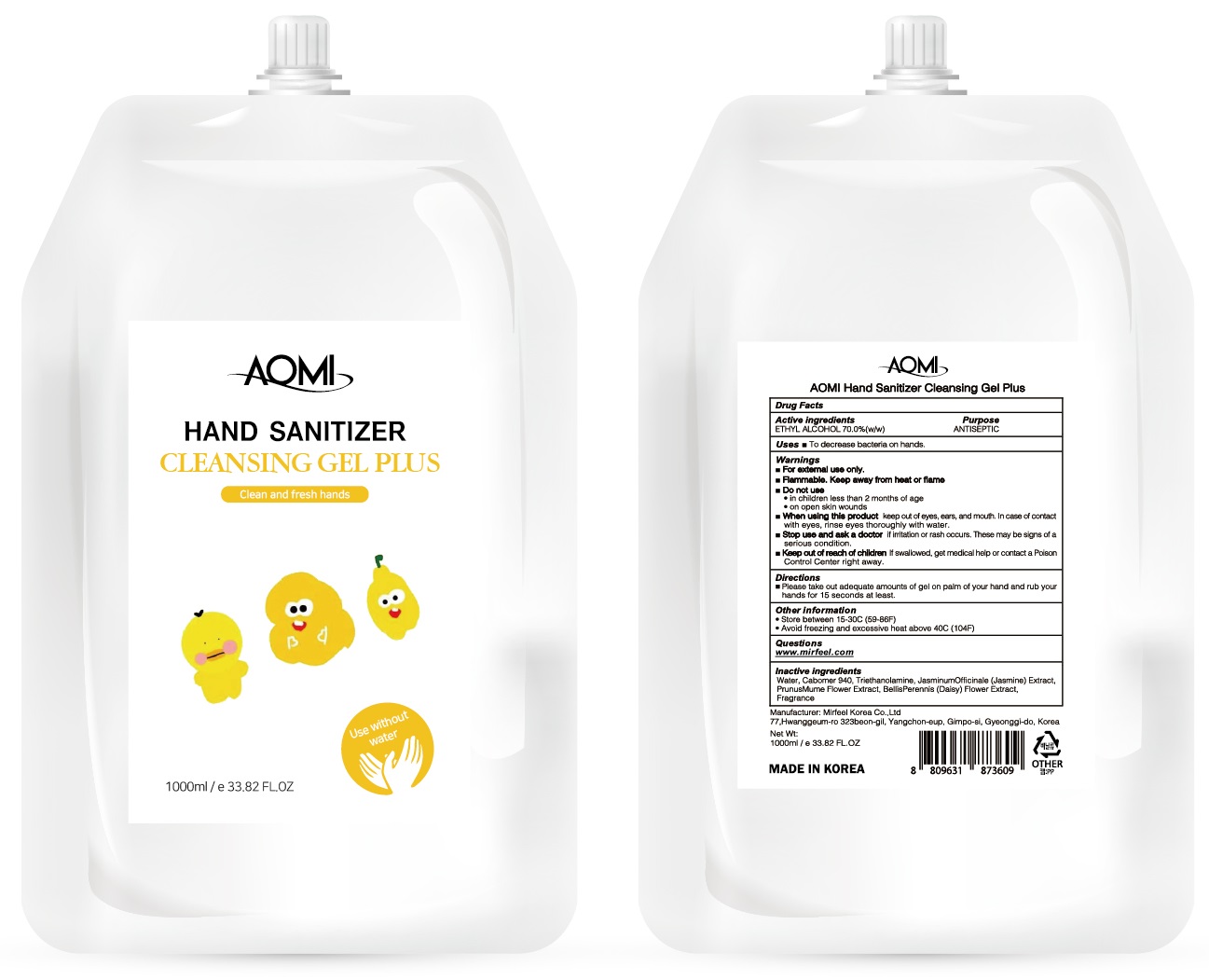 DRUG LABEL: Aomi Hand Sanitizer Cleansing Plus
NDC: 75010-140 | Form: GEL
Manufacturer: Mirfeel Korea Co., Ltd
Category: otc | Type: HUMAN OTC DRUG LABEL
Date: 20200915

ACTIVE INGREDIENTS: Alcohol 700 g/1000 mL
INACTIVE INGREDIENTS: Water; CARBOMER HOMOPOLYMER, UNSPECIFIED TYPE; TROLAMINE; JASMINUM OFFICINALE FLOWER; PRUNUS MUME FLOWER; BELLIS PERENNIS FLOWER

ACTIVE INGREDIENT

ETHYL ALCOHOL 70.0% (w/w)

INACTIVE INGREDIENTS

Water, Carbomer 940, Triethanolamine, Jasminum Officinale (Jasmine) Extract, Prunus Mume Flower Extract, Bellis Perennis (Daisy) Flower Extract, Fragrance

PURPOSE

ANTISEPTIC

WARNINGS

For external use only.

Flammable. Keep away from heat or flame

--------------------------------------------------------------------------------------------------------
Do not use
• in children less than 2 months of age
• on open skin wounds
--------------------------------------------------------------------------------------------------------
When using this product keep out of eyes, ears, and mouth. In case of contact with eyes, rinse eyes thoroughly with water.
--------------------------------------------------------------------------------------------------------
Stop use and ask a doctor if irritation or rash occurs. These may be signs of a serious condition.

Keep out of reach of children. If swallowed, get medical help or contact a Poison Control Center right away.

Uses

To decrease bacteria on hands

Directions

■ Please take out adequate amounts of gel on palm of your hand and rub your hands for 15 seconds at least.

Other Information

• Store between 15-30C (59-86F)

• Avoid freezing and excessive heat above 40C (104F)

QUESTIONS

www.mirfeel.com